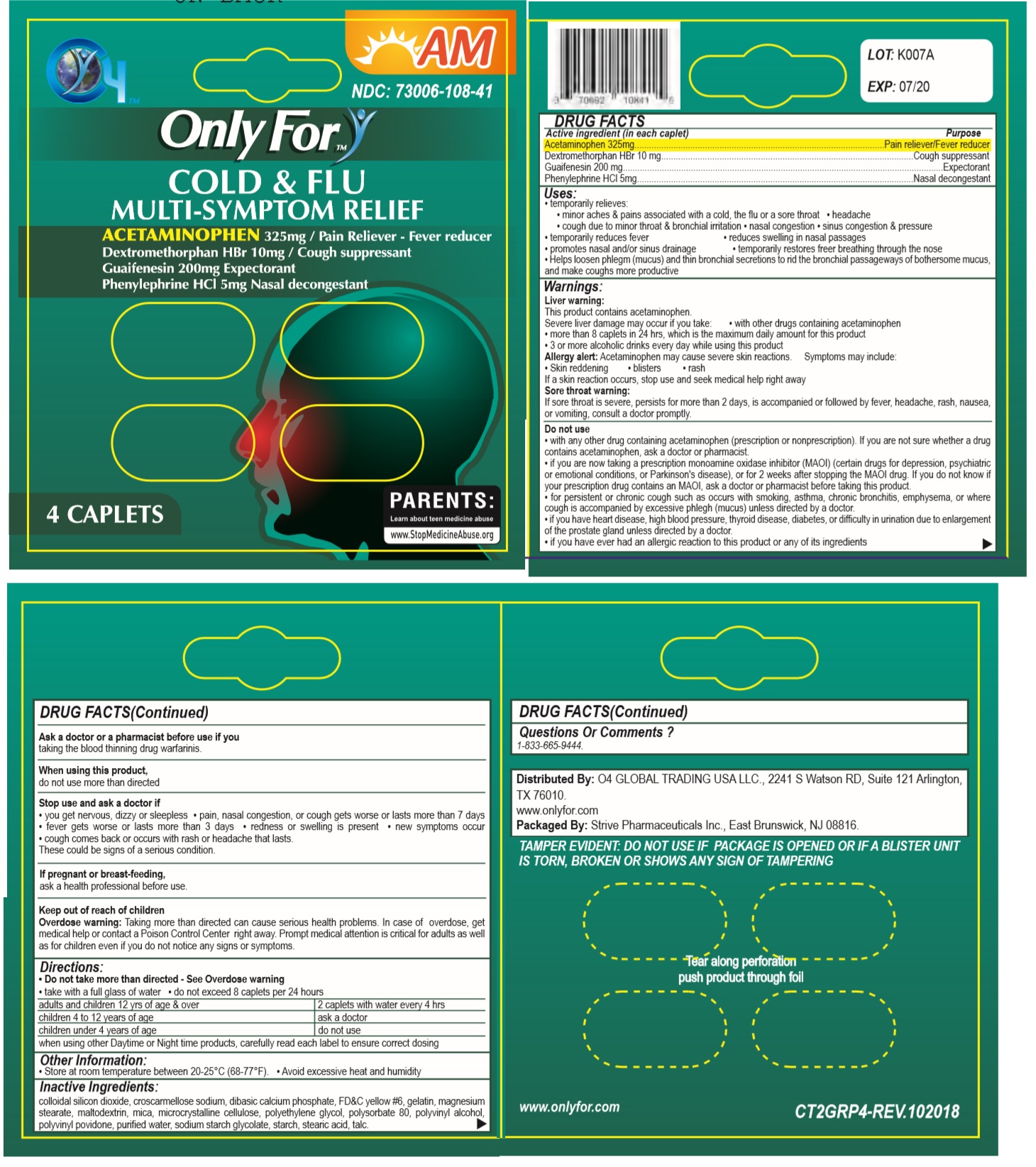 DRUG LABEL:  Only For 
NDC: 73006-108 | Form: TABLET
Manufacturer: O4 Global Trading Usa, Llc 
Category: otc | Type: HUMAN OTC DRUG LABEL
Date: 20190528

ACTIVE INGREDIENTS: ACETAMINOPHEN 325 mg/1 1; DEXTROMETHORPHAN HYDROBROMIDE 10 mg/1 1; GUAIFENESIN 200 mg/1 1; PHENYLEPHRINE HYDROCHLORIDE 5 mg/1 1
INACTIVE INGREDIENTS: SILICON DIOXIDE; CROSCARMELLOSE SODIUM; DIBASIC CALCIUM PHOSPHATE DIHYDRATE; FD&C YELLOW NO. 6; GELATIN, UNSPECIFIED; MAGNESIUM PALMITOSTEARATE; MALTODEXTRIN; MICA; MICROCRYSTALLINE CELLULOSE 101; POLYETHYLENE GLYCOL 400; POLYSORBATE 80; POLYVINYL ALCOHOL (94000 MW); POVIDONE K15; WATER; SODIUM STARCH GLYCOLATE TYPE A POTATO; STARCH, CORN; STEARIC ACID; TALC

Only For- COLD & FLU COUGH SUPPRESSANT

Active ingredient (in each caplet)

Acetaminophen 325 mg
Dextromethorphan HBr 10 mg
Guaifenesin 200 mg
Phenylephrine HCl 5 mg

Purpose

Pain reliever/Fever reducer
Cough suppressant
Expectorant
Nasal decongestant

Uses:

• temporarily relieves:
• minor aches & pains associated with a cold, the flu or a sore throat • headache • cough due to minor throat & bronchial irritation • nasal congestion • sinus congestion & pressure
• temporarily reduces fever • reduces swelling in nasal passages
• promotes nasal and/or sinus drainage • temporarily restores free breathing through the nose
• Helps loosen phlegm (mucus) and thin bronchial secretions to rid the bronchial passageways of bothersome mucus, and make coughs more productive

Warnings:

Liver warning:
This product contains acetaminophen.
Severe liver damage may occur if you take: • with other drugs containing acetaminophen
• more than 8 caplets in 24 hrs, which is the maximum daily amount for this product
• 3 or more alcoholic drinks every day while using this product

Allergy alert: Acetaminophen may cause severe skin reactions. Symptoms may include:
• Skin reddening • blisters • rash
If a skin reaction occurs, stop use and seek medical help right away

Sore throat warning:
If sore throat is severe, persists for more than 2 days, is accompanied or followed by fever, headache, rash, nausea, or vomiting, consult a doctor promptly.

Do not use
• with any other drug containing acetaminophen (prescription or nonprescription). If you are not sure whether a drug contains acetaminophen, ask a doctor or pharmacist.
• if you are now taking a prescription monoamine oxidase inhibitor (MAOI) (certain drugs for depression, psychiatric or emotional conditions, or Parkinson's disease), or for 2 weeks after stopping the MAOI drug. If you do not know if your prescription drug contains an MAOI, ask a doctor or pharmacist before taking this product.
• for persistent or chronic cough such as occurs with smoking, asthma, chronic bronchitis, emphysema, or where cough is accompanied by excessive phlegm (mucus) unless directed by a doctor.
• if you have heart disease, high blood pressure, thyroid disease, diabetes, or difficulty in urination due to enlargement of the prostate gland unless directed by a doctor.
• if you have ever had an allergic reaction to this product or any of its ingredients

Do not use, ask a doctor if you have
• liver disease • heart disease • high blood pressure • thyroid disease • diabetes
• trouble urinating due to an enlarged prostate gland • cough that occurs with too much phlegm (mucus) • persistent or chronic cough such as occurs with smoking, asthma, chronic bronchitis, or emphysema

Ask a doctor or a pharmacist before use if you
taking the blood thinning drug warfarinis.

When using this product,
do not use more than directed

Stop use and ask a doctor if
• you get nervous, dizzy or sleepless • pain, nasal congestion, or cough gets worse or lasts more than 7 days • fever gets worse or lasts more than 3 days • redness or swelling is present • new symptoms occur • cough comes back or occurs with rash or headache that lasts.
These could be signs of a serious condition.

If pregnant or breast-feeding,
ask a health professional before use.

Keep out of reach of children

Overdose warning: Taking more than directed can cause serious health problems. In case of overdose, get medical help or contact a Poison Control Center right away. Prompt medical attention is critical for adults as well as for children even if you do not notice any signs or symptoms.

Directions:

- Do not take more than directed - See Overdose warning
- take with a full glass of water • do not exceed 8 caplets per 24 hours

adults and children 12 yrs of age & over | 2 caplets with water every 4 hrs
children 4 to 12 years of age | ask a doctor
children under 4 years of age | do not use

when using other Daytime or Night time products, carefully read each label to ensure correct dosing

Other Information:

• Store at room temperature between 20-25°C (68-77°F). • Avoid excessive heat and humidity

Inactive Ingredients:

colloidal silicon dioxide, croscarmellose sodium, dibasic calcium phosphate, FD&C yellow #6, gelatin, magnesium stearate, maltodextrin, mica, microcrystalline cellulose, polyethylene glycol, polysorbate 80, polyvinyl alcohol, polyvinyl povidone, purified water, sodium starch glycolate, starch, stearic acid, talc.

Questions Or Comments ?

1-833-665-9444.

NDC: 73006-108-41

READ AND KEEP OUTER PACKAGE FOR COMPLETE PRODUCT INFORMATION.

Distributed By: O4 GLOBAL TRADING USA LLC., 2241 S Watson RD, Suite 121 Arlington, TX 76010.

www.onlyfor.com

Packaged By: Strive Pharmaceuticals Inc., East Brunswick, NJ 08816.

TAMPER EVIDENT: DO NOT USE IF PACKAGE IS OPENED OR IF A BLISTER UNIT IS TORN, BROKEN OR SHOWS ANY SIGN OF TAMPERING

Tear along perforation push product through foil